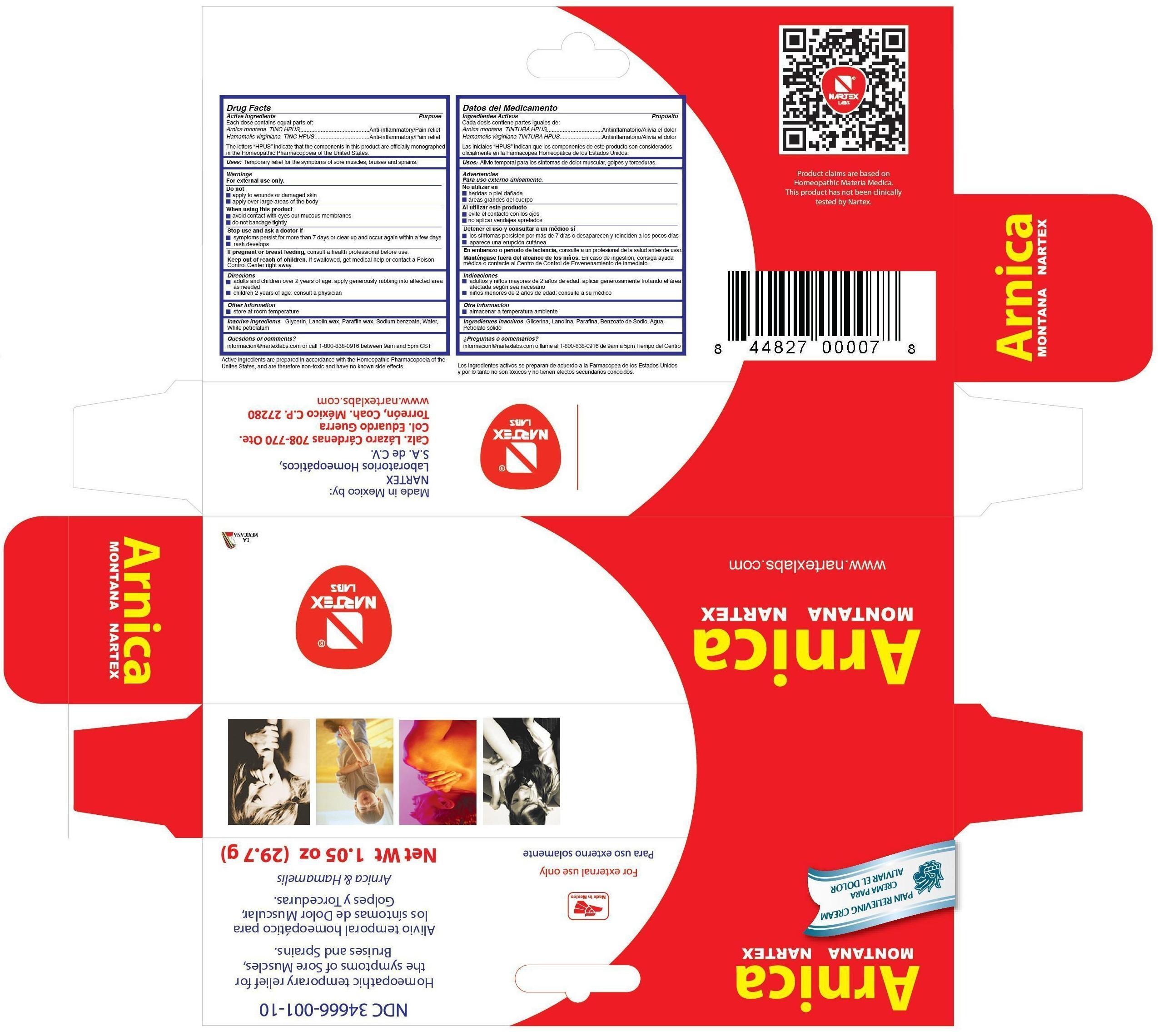 DRUG LABEL: Arnica Montana Nartex
NDC: 34666-001 | Form: CREAM
Manufacturer: NARTEX LABORATORIOS HOMEOPATICOS SA DE CV
Category: homeopathic | Type: HUMAN OTC DRUG LABEL
Date: 20251211

ACTIVE INGREDIENTS: ARNICA MONTANA 1.73 g/29.7 g; HAMAMELIS VIRGINIANA LEAF 0.0178 g/29.7 g
INACTIVE INGREDIENTS: PETROLATUM; LANOLIN; GLYCERIN; PARAFFIN; SODIUM BENZOATE; WATER

Drug Facts

Active Ingredients

Each dose contains equal parts of:

Arnica montana TINC HPUS

Hamamelis virginiana TINC HPUS

The letters "HPUS" indicate that the components in this product are officially monographed in the Homeopathic Pharmacopoeia of the Untied States.

Purpose

Arnica montana TINC HPUS......................Anti-inflammatory/Pain relief
Hamamelis virginiana TINC HPUS.............Anti-inflammatory/Pain relief

Uses:

Temporary relief for the symptoms of sore muscles, bruises and sprains.

Warnings

For external use only.

Do not

- apply to wounds or damaged skin
- apply over large areas of the body

When using this product

- avoid contact with eyes or mucous membranes
- do not bandage tightly

Stop use and ask a doctor if

- symptoms persist for more than 7 days or clear up and occur again within a few days
- rash develops

PREGNANCY OR BREAST FEEDING

If pregnant or breast feeding,consult a health professional before use.

Keep out of reach of children.

OTHER SAFETY INFORMATION

If swallowed, get medical help or contact a Poison Control Center right away.

Directions

- adults and children over 2 years of age: apply generously rubbing into affected area as needed
- children 2 years of age: consult a physician

Other information

- store at room temperature

Inactive ingredients

Glycerin, Lanolin wax, Paraffin wax, Sodium benzoate, Water, White petrolatum

Questions or comments?

informacion@nartexlabs.com or call 1-800-838-0916 between 9am and 5pm CST

DESCRIPTION

Active ingredients are prepared in accordance with the Homeopathic Pharmacopoeia of the United States, and are therefore non-toxic and have no known side effects.
Product claims are based on Homeopathic Materia Medica. This product has not been clinically tested by Nartex.
Made in Mexico by:
NARTEX
Laboratorios Homeopaticos,
S.A. de C.V.
Calz. Lazaro Cardenas 708-770 Ote.
Col. Eduardo Guerra
Torreon, Coah. Mexico C.P. 27280
www.nartexlabs.com

Principal Display Panel

For external use only
Para uso externo solamente
NDC 34666-001-10
Homeopathic temporary relief for
the symptoms of Sore Muscles,
Bruises and Sprains.
Alivio temporal homeopatico para
los sintomas de Dolor Muscular,
Golpes y Torceduras.
Arnica and Hamamelis
Net Wt 1.05 oz (29.7 g)